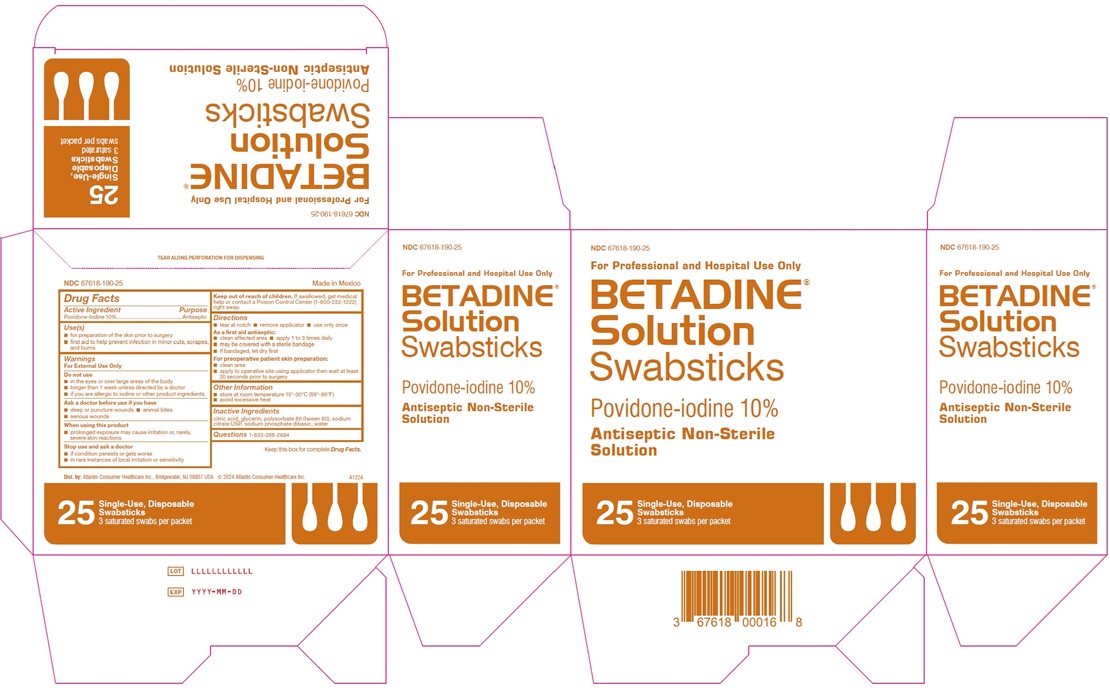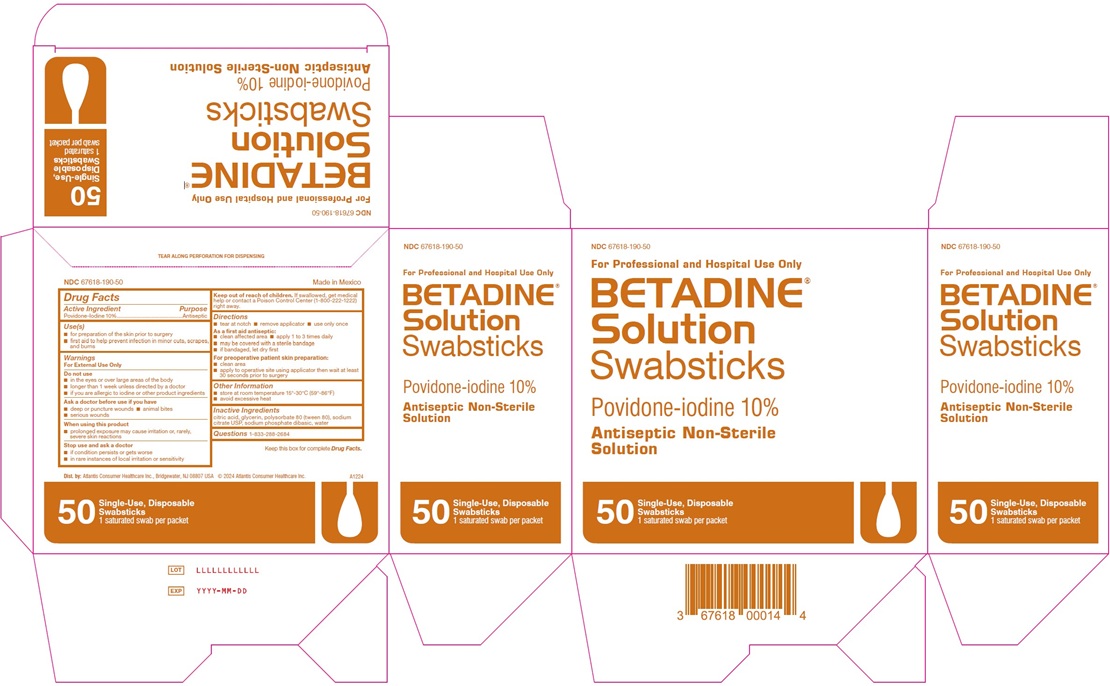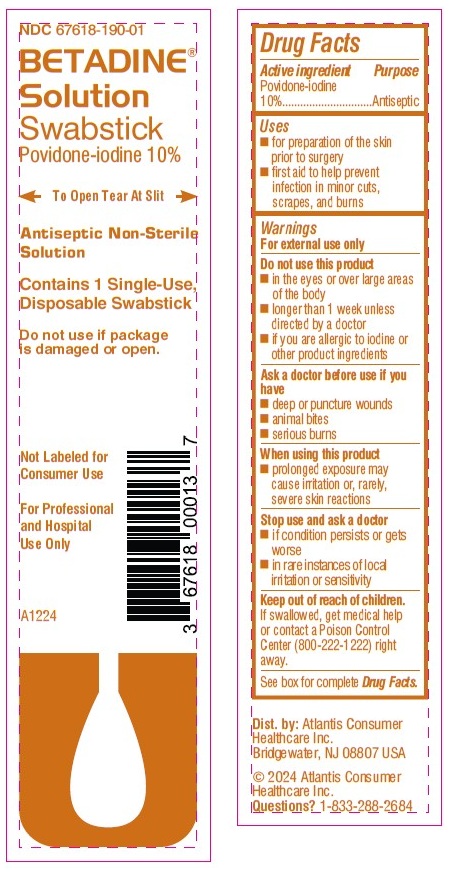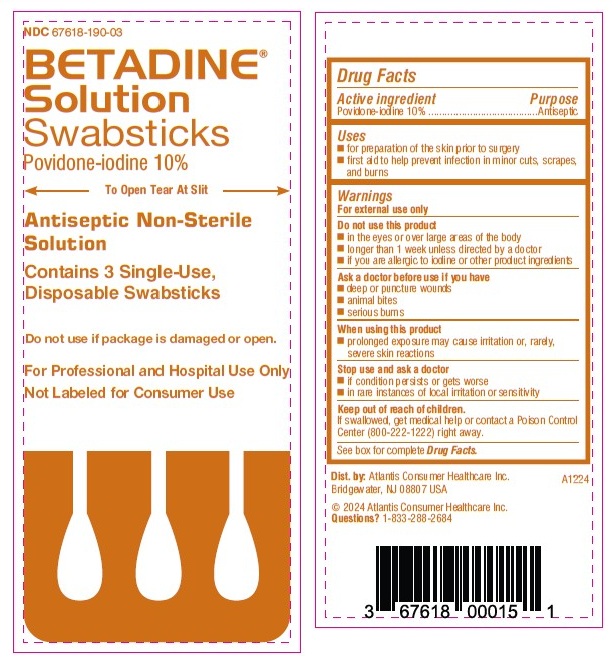 DRUG LABEL: Betadine
NDC: 67618-190 | Form: SOLUTION
Manufacturer: Atlantis Consumer Healthcare, Inc.
Category: otc | Type: HUMAN OTC DRUG LABEL
Date: 20250214

ACTIVE INGREDIENTS: POVIDONE-IODINE 100 mg/1 mL
INACTIVE INGREDIENTS: Citric Acid Monohydrate; Glycerin; Polysorbate 80; Sodium Citrate, Unspecified Form; Sodium Phosphate, Dibasic, Unspecified Form; Water

BETADINE® Professional Solution Swabsticks
Povidone-iodine 10%
Drug Facts

Active ingredient

Povidone-iodine 10%

Purpose

Antiseptic

Use(s)

- for preparation of the skin prior to surgery
- first aid to help prevent infection in minor cuts, scrapes, and burns

Warnings

For external use only

Do not use

- in the eyes or over large areas of the body
- longer than 1 week unless directed by a doctor
- if you are allergic to iodine or other product ingredients

Ask a doctor before use if you have

- deep or puncture wounds
- animal bites
- serious wounds

When using this product

- prolonged exposure may cause irritation or, rarely, severe skin reactions

Stop use and ask a doctor

- if condition persists or gets worse
- in rare instances of local irritation or sensitivity

Keep out of reach of children.

If swallowed, get medical help or contact a Poison Control Center (1-800-222-1222) right away.

Directions

- tear at notch
- remove applicator
- use only once

As a first aid antiseptic:

- clean affected area
- apply 1 to 3 times daily
- may be covered with a sterile bandage
- if bandaged, let dry first

For preoperative patient skin preparation:

- clean area
- apply to operative site using applicator then wait at least 30 seconds prior to surgery

Other Information

- store at room temperature 15°-30°C (59°-86°F)
- avoid excessive heat

Inactive Ingredients

citric acid, glycerin, polysorbate 80 (tween 80), sodium citrate USP, sodium phosphate dibasic, water

Questions

1-833-288-2684
Dist. by: Atlantis Consumer
Healthcare Inc.
Bridgewater, NJ 08807 USA
©2024 Atlantis Consumer
Healthcare Inc.

PACKAGE LABEL.PRINCIPAL DISPLAY PANEL

NDC 67618-190-01
BETADINE®
SOLUTION
Swabsticks
Povidone-iodine 10%
To Open Tear At Slit
Antiseptic Non-Sterile
Solution
Contains 1 Single-Use,
Disposable Swabstick
Do not use if package
is damaged or open.
Not Labeled for
Consumer Use
For Professional
and Hospital
Use Only
A1224
Dist. by: Atlantis Consumer
Healthcare Inc.
Bridgewater, NJ 08807 USA
See box for complete Drug Facts
©2024 Atlantis Consumer
Healthcare Inc.
Questions? 1-833-288-2684

NDC 67618-190-50
For Professional and Hospital Use Only
BETADINE®
SOLUTION
Swabsticks
Povidone-iodine 10%
Antiseptic Non-Sterile
Solution
50
Single-use, Disposable
Swabsticks
1 saturated swab per packet
LOT LLLLLLLLLLLL
EXP YYYY-MM-DD

NDC 67618-190-03
BETADINE®
SOLUTION
Swabsticks
Povidone-iodine 10%
To Open Tear At Slit
Antiseptic Non-Sterile
Solution
Contains 3 Single-Use,
Disposable Swabstick
Do not use if package is damaged or open.
For Professional and Hospital Use Only
Not Labeled for Consumer Use
See box for complete Drug Facts
Dist. by: Atlantis Consumer Healthcare Inc.
Bridgewater, NJ 08807 USA
A1224
©2024 Atlantis Consumer Healthcare Inc.
Questions? 1-833-288-2684

NDC 67618-190-25
For Professional and Hospital Use Only
BETADINE®
SOLUTION
Swabsticks
Povidone-iodine 10%
Antiseptic Non-Sterile
Solution
25
Single-use, Disposable
Swabsticks
3 saturated swabs per packet
LOT LLLLLLLLLLLL
EXP YYYY-MM-DD